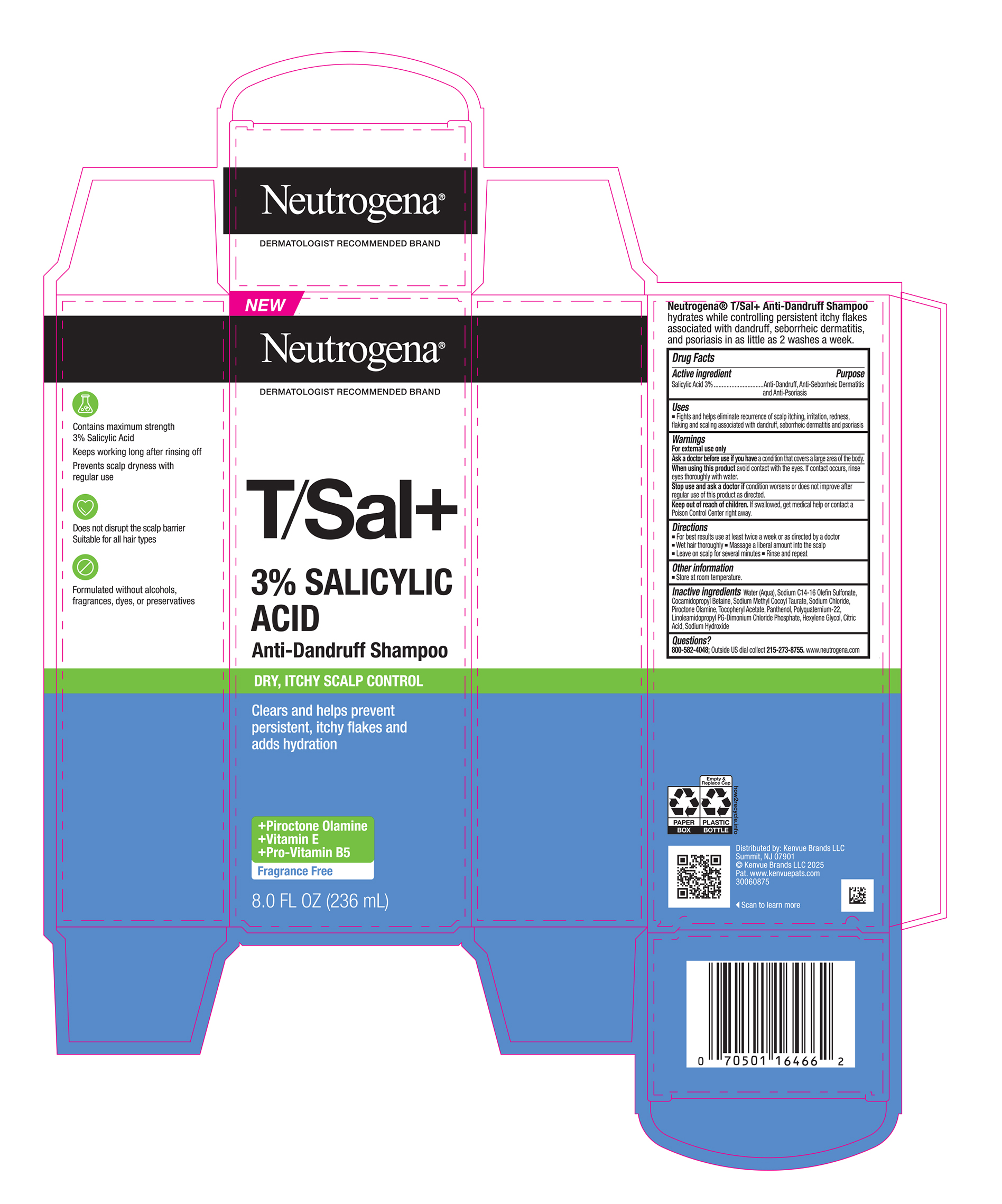 DRUG LABEL: Neutrogena T/Sal Plus 3% Salicylic Acid Anti-Dandruff for Dry, Itchy Scalp Control
NDC: 69968-0939 | Form: SHAMPOO
Manufacturer: Kenvue Brands LLC
Category: otc | Type: HUMAN OTC DRUG LABEL
Date: 20251222

ACTIVE INGREDIENTS: SALICYLIC ACID 30 mg/1 mL
INACTIVE INGREDIENTS: WATER; SODIUM C14-16 OLEFIN SULFONATE; COCAMIDOPROPYL BETAINE; SODIUM CHLORIDE; HEXYLENE GLYCOL; LINOLEAMIDOPROPYL PROPYLENE GLYCOL-DIMONIUM CHLORIDE PHOSPHATE; SODIUM HYDROXIDE; CITRIC ACID MONOHYDRATE; PANTHENOL; ALPHA-TOCOPHEROL ACETATE; PIROCTONE OLAMINE; SODIUM METHYL COCOYL TAURATE

Neutrogena T/Sal + 3% Salicylic Acid Anti-Dandruff Shampoo for Dry, Itchy Scalp Control

Drug Facts

Active ingredient

Salicylic Acid (3%)

Purpose

Anti-Dandruff, Anti-Seborrheic Dermatitis and Anti-Psoriasis

Uses

▪ Fights and helps eliminate recurrence of scalp itching, irritation, redness, flaking and scaling associated with dandruff, seborrheic dermatitis and psoriasis

Warnings

For external use only

Ask a doctor before use if you have a condition that covers a large area of the body.

When using this product avoid contact with the eyes. If contact occurs, rinse eyes thoroughly with water.

Stop use and ask a doctor if condition worsens or does not improve after regular use of this product as directed.

Keep out of reach of children. If swallowed, get medical help or contact a Poison Control Center right away.

Directions

▪ For best results use at least twice a week or as directed by a doctor

▪ Wet hair thoroughly

▪ Massage a liberal amount into the scalp

▪ Leave on scalp for several minutes

▪ Rinse and repeat

Other information

Store at room temperature.

Inactive ingredients

Water (Aqua), Sodium C14-16 Olefin Sulfonate, Cocamidopropyl Betaine, Sodium Methyl Cocoyl Taurate, Sodium Chloride, Piroctone Olamine, Tocopheryl Acetate, Panthenol, Polyquaternium-22, Linoleamidopropyl PG-Dimonium Chloride Phosphate, Hexylene Glycol, Citric Acid, Sodium Hydroxide

Questions?

800-582-4048; Outside US dial collect 215-273-8755. www.neutrogena.com

Distributed by:
Kenvue Brands LLC
Summit, NJ 07901

PRINCIPAL DISPLAY PANEL - 236 mL Bottle Carton

NEW

Neutrogena®

DERMATOLOGIST RECOMMENDED BRAND

T/Sal+

3% SALICYLIC

ACID

Anti-Dandruff Shampoo

DRY, ITCHY SCALP CONTROL

Clears and helps prevent

persistent, itchy flakes and

adds hydration

+ Piroctone Olamine

+ Vitamin E

+ Pro-Vitamin B5

Fragrance Free

8.0 FL OZ (236 mL)